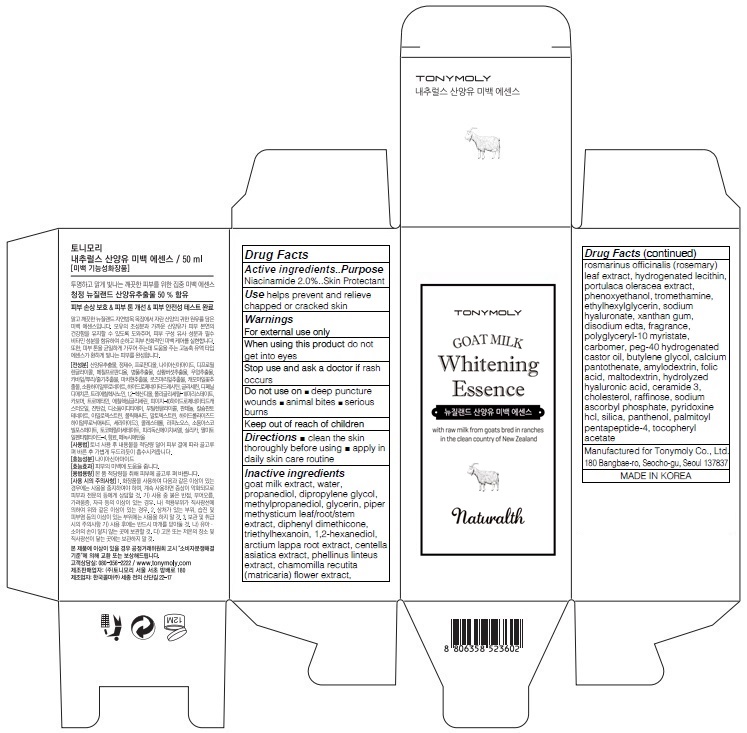 DRUG LABEL: TONYMOLY NATURALTH GOAT MILK WHITENING ESSENCE
NDC: 59078-260 | Form: CREAM
Manufacturer: TONYMOLY CO.,LTD
Category: otc | Type: HUMAN OTC DRUG LABEL
Date: 20160122

ACTIVE INGREDIENTS: Niacinamide 1.0 g/50 mL
INACTIVE INGREDIENTS: goat milk; water

ACTIVE INGREDIENT

Active ingredients: Niacinamide 2.0%

INACTIVE INGREDIENT

Inactive ingredients: goat milk extract, water, propanediol, dipropylene glycol, methylpropanediol, glycerin, piper methysticum leaf/root/stem extract, diphenyl dimethicone, triethylhexanoin, 1,2-hexanediol, arctium lappa root extract, centella asiatica extract, phellinus linteus extract, chamomilla recutita (matricaria) flower extract, rosmarinus officinalis (rosemary) leaf extract, hydrogenated lecithin, portulaca oleracea extract, phenoxyethanol, tromethamine, ethylhexylglycerin, sodium hyaluronate, xanthan gum, disodium edta, fragrance, polyglyceryl-10 myristate, carbomer, peg-40 hydrogenated castor oil, butylene glycol, calcium pantothenate, amylodextrin, folic acid, maltodextrin, hydrolyzed hyaluronic acid, ceramide 3, cholesterol, raffinose, sodium ascorbyl phosphate, pyridoxine hcl, silica, panthenol, palmitoyl pentapeptide-4, tocopheryl acetate

PURPOSE

Purpose: Skin Protectant

WARNINGS

Warnings: For external use only

When using this product do not get into eyes

Stop use and ask a doctor if rash occurs

Do not use on - deep puncture wounds - animal bites - serious burns

Keep out of reach of children

KEEP OUT OF REACH OF CHILDREN

Use

Use: helps prevent and relieve chapped or cracked skin

Directions

Directions: - clean the skin thoroughly before using - apply in daily skin care routine